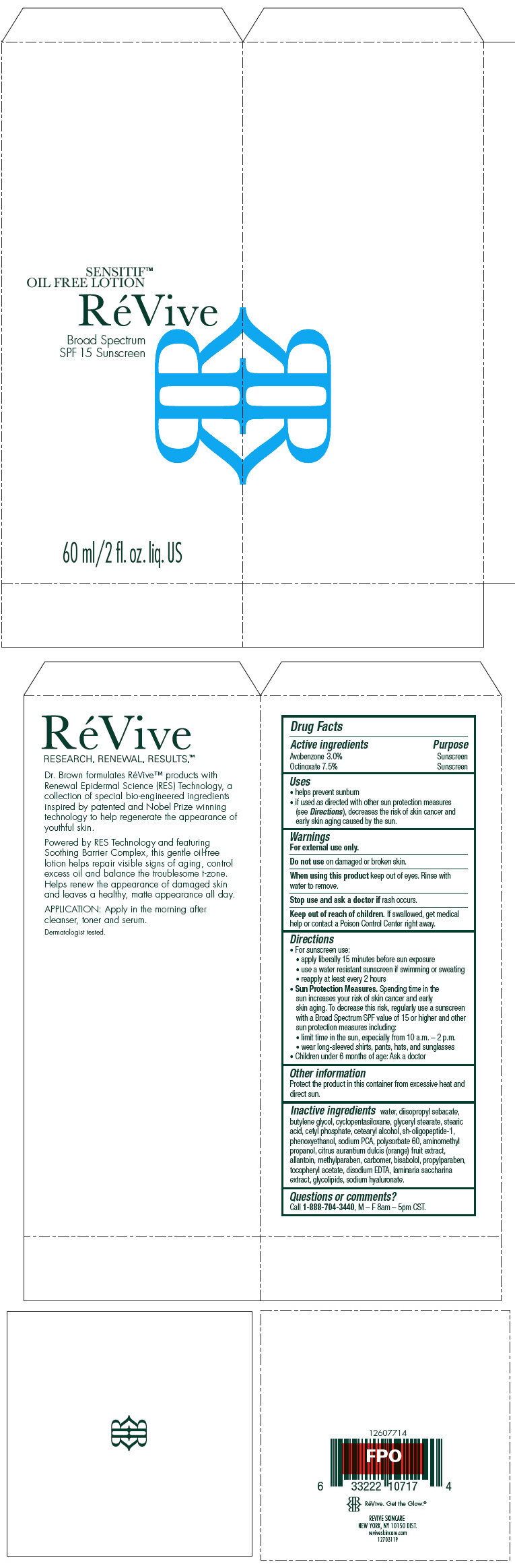 DRUG LABEL: ReVive Sensitif Oil Free 
NDC: 58411-418 | Form: CREAM
Manufacturer: RéVive Skincare
Category: otc | Type: HUMAN OTC DRUG LABEL
Date: 20180119

ACTIVE INGREDIENTS: AVOBENZONE 30 mg/1 mL; OCTINOXATE 75 mg/1 mL
INACTIVE INGREDIENTS: WATER; DIISOPROPYL SEBACATE; BUTYLENE GLYCOL; GLYCERYL MONOSTEARATE; STEARIC ACID; CETYL PHOSPHATE; CETOSTEARYL ALCOHOL; NEPIDERMIN; PHENOXYETHANOL; SODIUM PYRROLIDONE CARBOXYLATE; POLYSORBATE 60; AMINOMETHYLPROPANOL; ORANGE; ALLANTOIN; METHYLPARABEN; LEVOMENOL; PROPYLPARABEN; .ALPHA.-TOCOPHEROL ACETATE; EDETATE DISODIUM ANHYDROUS; HYALURONATE SODIUM

RéVive Sensitif™ Oil Free
Lotion Broad Spectrum SPF 15 Sunscreen

Drug Facts

ACTIVE INGREDIENT

Active ingredients | Purpose
Avobenzone 3.0% | Sunscreen
Octinoxate 7.5% | Sunscreen

Uses

- helps prevent sunburn
- if used as directed with other sun protection measures (see Directions), decreases the risk of skin cancer and early skin aging caused by the sun.

Warnings

For external use only.

Do not use on damaged or broken skin.

When using this product keep out of eyes. Rinse with water to remove.

Stop use and ask a doctor if rash occurs.

Keep out of reach of children. If swallowed, get medical help or contact a Poison Control Center right away.

Directions

- For sunscreen use:
  - apply liberally 15 minutes before sun exposure
  - use a water resistant sunscreen if swimming or sweating
  - reapply at least every 2 hours
- Sun Protection Measures. Spending time in the sun increases your risk of skin cancer and early skin aging. To decrease this risk, regularly use a sunscreen with a Broad Spectrum SPF value of 15 or higher and other sun protection measures including:
  - limit time in the sun, especially from 10 a.m. – 2 p.m.
  - wear long-sleeved shirts, pants, hats, and sunglasses
- Children under 6 months of age: Ask a doctor

Other information

Protect the product in this container from excessive heat and direct sun.

Inactive ingredients

water, diisopropyl sebacate, butylene glycol, cyclopentasiloxane, glyceryl stearate, stearic acid, cetyl phosphate, cetearyl alcohol, sh-oligopeptide-1, phenoxyethanol, sodium PCA, polysorbate 60, aminomethyl propanol, citrus aurantium dulcis (orange) fruit extract, allantoin, methylparaben, carbomer, bisabolol, propylparaben, tocopheryl acetate, disodium EDTA, laminaria saccharina extract, glycolipids, sodium hyaluronate.

Questions or comments?

Call 1-888-704-3440, M – F 8am – 5pm CST.

PRINCIPAL DISPLAY PANEL - 60 ml Bottle Carton

SENSITIF™
OIL FREE LOTION

RéVive

Broad Spectrum
SPF 15 Sunscreen

60 ml/2 fl. oz. liq. US